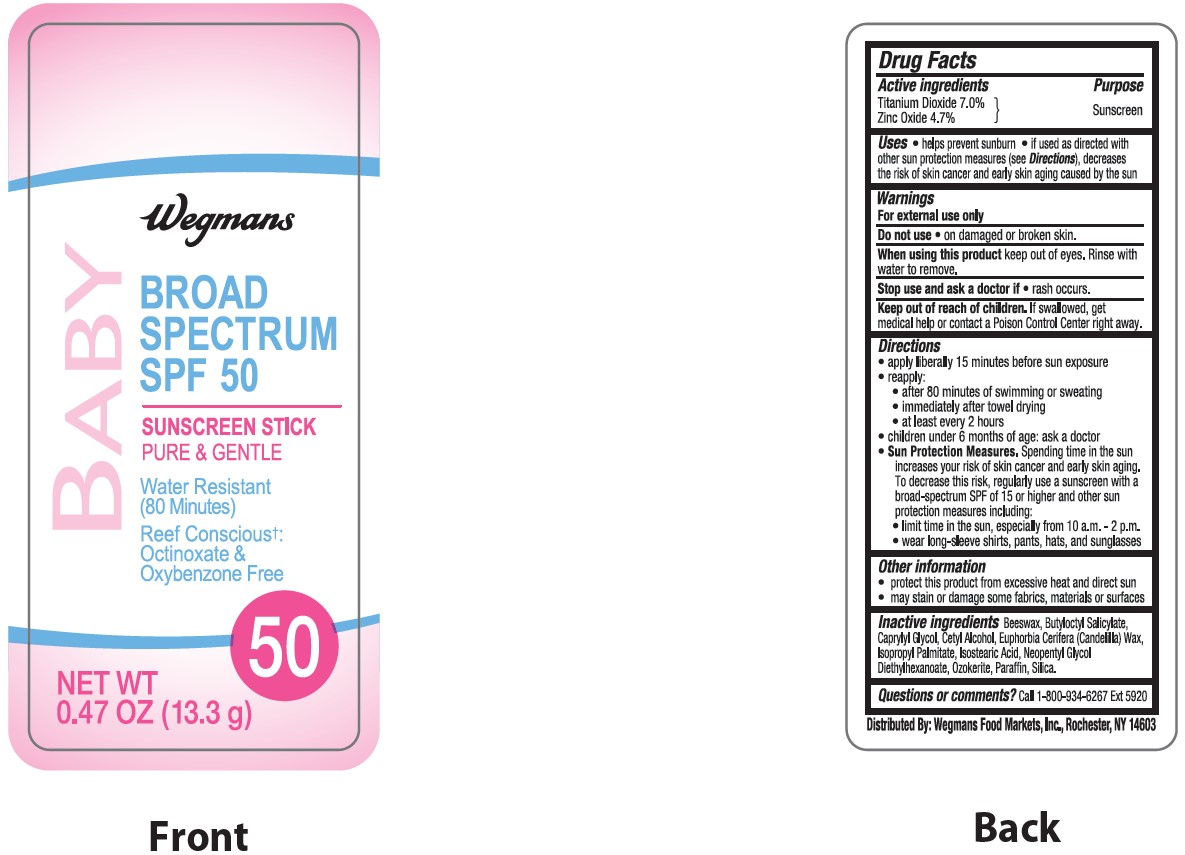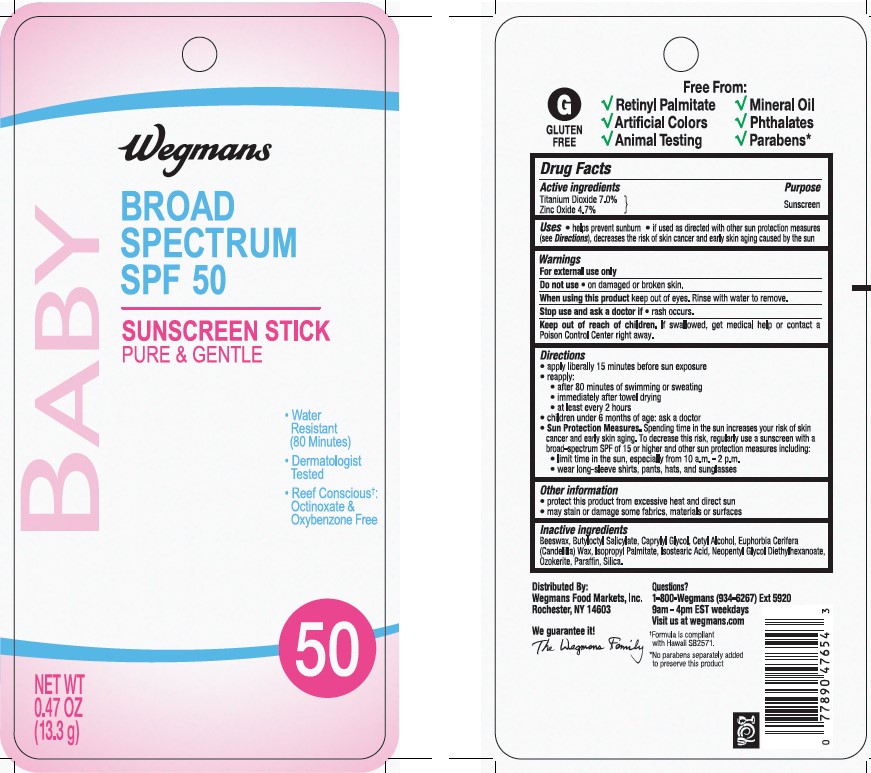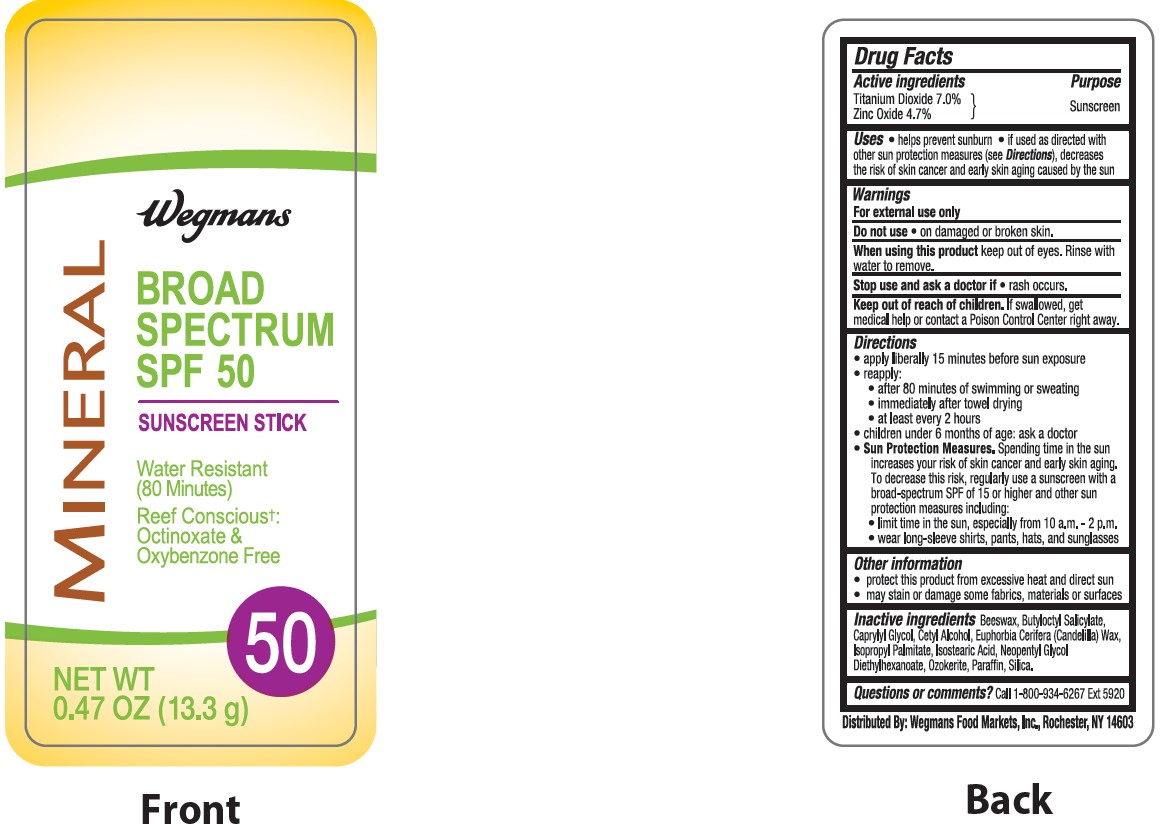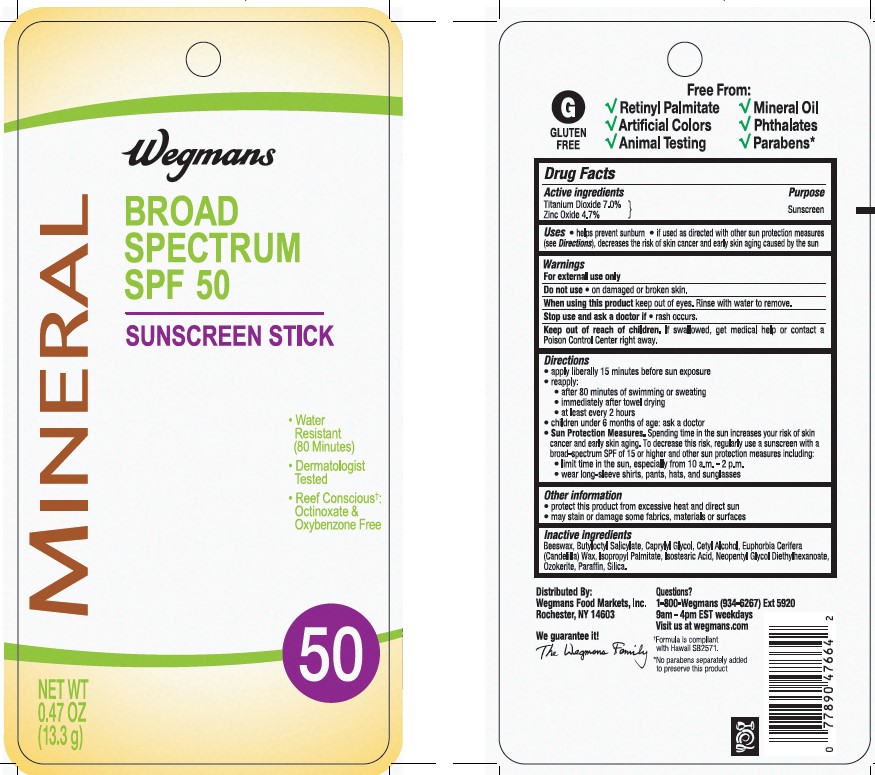 DRUG LABEL: MINERAL SUNSCREEN SPF 50
NDC: 47124-120 | Form: STICK
Manufacturer: WEGMANS FOOD MARKETS INC
Category: otc | Type: HUMAN OTC DRUG LABEL
Date: 20241016

ACTIVE INGREDIENTS: TITANIUM DIOXIDE 70 mg/1 g; ZINC OXIDE 47 mg/1 g
INACTIVE INGREDIENTS: ISOPROPYL PALMITATE; BUTYLOCTYL SALICYLATE; CETYL ALCOHOL; CANDELILLA WAX; NEOPENTYL GLYCOL DIETHYLHEXANOATE; CERESIN; WHITE WAX; CAPRYLYL GLYCOL; ISOSTEARIC ACID; PARAFFIN; SILICON DIOXIDE

WEGMANS MINERAL SUNSCREEN STICK SPF 50

Active ingredients

Titanium Dioxide 7.0%, Zinc Oxide 4.7%

Purpose

Sunscreen

Uses

- helps prevent sunburn
- if used as directed with other sun protection measures (see Directions), decreases the risk of skin cancer and early skin aging caused by the sun

Warnings

For external use only

Do not use

- on damaged or broken skin.

When using this product

- keep out of eyes. Rinse with water to remove.

Stop use and ask a doctor if

- rash occurs.

Keep out of reach of children.

If swallowed, get medical help or contact a Poison Control Center right away.

Directions

- apply liberally 15 minutes before sun exposure
- reapply:
  - after 80 minutes of swimming or sweating
  - immediately after towel drying
  - at least every 2 hours
  - children under 6 months of age: Ask a doctor
  - Sun Protection Measures. Spending time in the sun increases your risk of skin cancer and early skin aging. To decrease this risk, regularly use a sunscreen with a Broad Spectrum SPF value of 15 or higher and other sun protection measures including:
  - limit time in the sun, especially from 10 a.m.-2 p.m.
  - wear long-sleeved shirts, pants, hats, and sunglasses

Other information

- protect this product in this container from excessive heat and direct sun
- may stain or damage some fabrics, materials or surfaces

Inactive ingredients

beeswax, butyloctyl salicylate, caprylyl glycol, cetyl alcohol, euphorbia cerifera (candelilla) wax, isopropyl palmitate, isostearic acid, neopentyl glycol diethylhexanoate, ozokerite, paraffin, silica